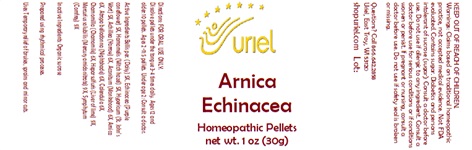 DRUG LABEL: Arnica Echinacea
NDC: 48951-1381 | Form: PELLET
Manufacturer: Uriel Pharmacy Inc
Category: homeopathic | Type: HUMAN OTC DRUG LABEL
Date: 20241202

ACTIVE INGREDIENTS: BELLIS PERENNIS 5 [hp_X]/1 1; ECHINACEA, UNSPECIFIED 5 [hp_X]/1 1; HAMAMELIS VIRGINIANA ROOT BARK/STEM BARK 5 [hp_X]/1 1; ST. JOHN'S WORT 5 [hp_X]/1 1; ACHILLEA MILLEFOLIUM 6 [hp_X]/1 1; ACONITUM NAPELLUS 6 [hp_X]/1 1; ARNICA MONTANA 6 [hp_X]/1 1; ATROPA BELLADONNA 6 [hp_X]/1 1; CALENDULA OFFICINALIS FLOWERING TOP 6 [hp_X]/1 1; MATRICARIA RECUTITA 6 [hp_X]/1 1; CALCIUM SULFIDE 9 [hp_X]/1 1; MERCURIUS SOLUBILIS 9 [hp_X]/1 1; COMFREY ROOT 9 [hp_X]/1 1
INACTIVE INGREDIENTS: SUCROSE

Arnica Echinacea

INDICATIONS AND USAGE

Directions: FOR ORAL USE ONLY.

DOSAGE AND ADMINISTRATION

Dissolve pellets under the tongue 3-4 times daily. Ages 12 and older: 10 pellets. Ages 2-11: 5 pellets. Under age 2: Consult a doctor.

ACTIVE INGREDIENT

Active Ingredients: Bellis per. (Daisy) 5X, Echinacea (Purple coneflower) 5X, Hamamelis (Witch hazel) 5X, Hypericum (St. John’s Wort) 5X, Achillea (Yarrow) 6X, Aconitum (Monkshood) 6X, Arnica 6X, Atropa belladonna (Nightshade) 6X, Calendula 6X, Chamomilla (Chamomile) 6X, Hepar sulfuris (Liver of lime) 9X, Mercurius solubilis (Mercury amidonitrate) 9X, Symphytum (Comfrey) 9X

Inactive Ingredients: Organic sucrose

Prepared using rhythmical processes.

PURPOSE

Uses: Temporary relief of bruises, sprains and minor cuts.

KEEP OUT OF REACH OF CHILDREN.

WARNINGS

Warnings: Claims based on traditional homeopathic practice, not accepted medical evidence. Not FDA evaluated. Contains sugar. Diabetics and persons intolerant of sucrose (sugar): Consult a doctor before use. Do not use if allergic to any ingredient. Contains traces of lactose. Consult a doctor before use for serious conditions or if conditions worsen or persist. If pregnant or nursing, consult a doctor before use. Do not use if safety seal is broken or missing.

Questions? Call 866.642.2858
Uriel, East Troy, WI 53120
shopuriel.com Lot: